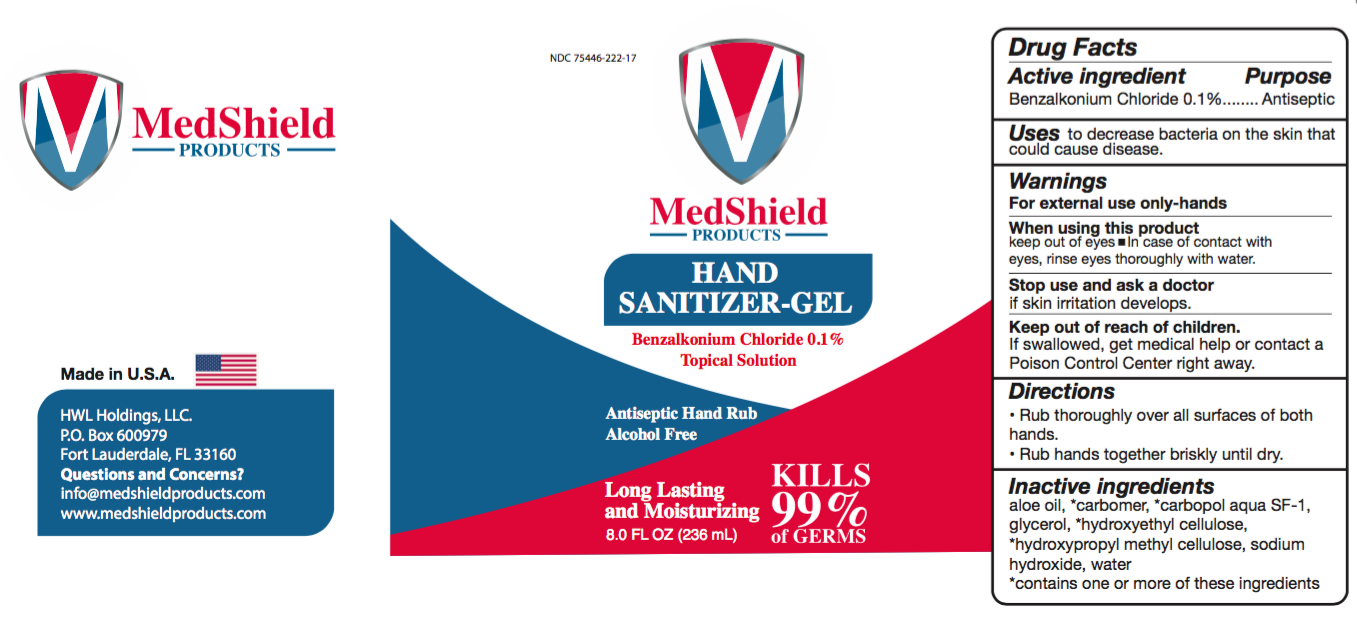 DRUG LABEL: MedShield Products
NDC: 75446-222 | Form: GEL
Manufacturer: HWL Holdings, LLC
Category: otc | Type: HUMAN OTC DRUG LABEL
Date: 20200425

ACTIVE INGREDIENTS: BENZALKONIUM CHLORIDE 1 ug/1 mL
INACTIVE INGREDIENTS: HYDROXYETHYL CELLULOSE, UNSPECIFIED; HYPROMELLOSES; METHACRYLIC ACID - ETHYL ACRYLATE COPOLYMER (4500 MPA.S); SODIUM HYDROXIDE; GLYCERIN; ALOE VERA LEAF; WATER; CARBOMER HOMOPOLYMER, UNSPECIFIED TYPE

MedShield Gel

Active Ingredient(s)

Benzalkonium Chloride 0.1% Purpose: Antiseptic

Purpose

Antiseptic, Hand Sanitizer

Use

to decrease bacteria on the skin that could cause disease

Warnings

For external use only-hands

WHEN USING

keep out of eyes In case of contact with eyes, rinse eyes thoroughly with water.

STOP USE

if skin irritation develops.

Keep out of reach of children. If swallowed, get medical help or contact a Poison Control Center right away.

Directions

- Rub thoroughly over all surfaces of both hands.
- Rub hands together briskly until dry.

Other information

- Store between 15-30C (59-86F)
- Avoid freezing and excessive heat above 40C (104F)

Inactive ingredients

aloe oil, *carbomer, *carbopol aqua SF-1, glycerol, *hydroxyethyl cellulose, *hydroxypropyl methyl cellulose, sodium hydroxide, water

*contains one or more of these ingredients

Package Label - Principal Display Panel

236 mL NDC: 75446-222-17